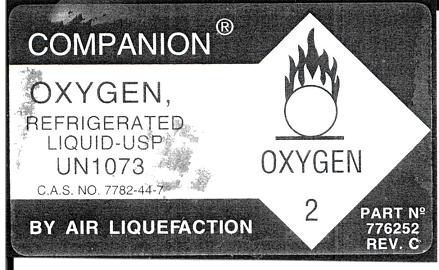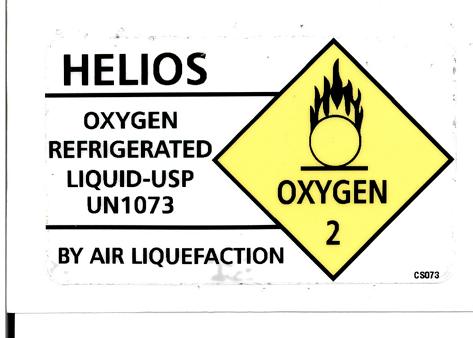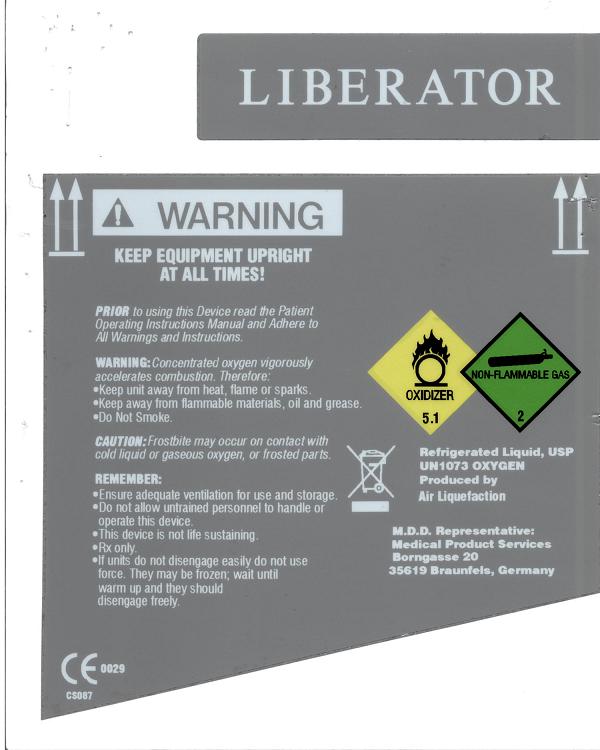 DRUG LABEL: OXYGEN
NDC: 59714-101 | Form: LIQUID
Manufacturer: AIRWAY OXYGEN INC
Category: prescription | Type: HUMAN PRESCRIPTION DRUG LABEL
Date: 20100617

ACTIVE INGREDIENTS: OXYGEN 99 L/100 L

Liquid Oxygen

PACKAGE LABEL

LIBERATOR
WARNING
KEEP EQUIPMENT UPRIGHT
AT ALL TIMES
PRIORto using this Device read the Patient
Operating Instructions Manual and Adhere to
All Warnings and Instructions.
WARNING: Concentrated oxygen vigorously
accelerates combustion. Therefore:
Keep unit away from heat, flame or sparks.
Keep away from flammable materials, oil and grease.
Do Not Smoke.
CAUTION: Frostbite may occur on contact with
cold liquid or gaseous oxygen, or frosted parts.
REMEMBER:
Ensure adequate ventilation for use and storage.
Do not allow untrained personnel to handle or
operate this device
This device is not life sustaining.
Rx only.
If units do not disengage easily do not use
force. They may be frozen; wait until
warm up and they should
disengage freely.
OXIDIZER
5.1
NON-FLAMMABLE GAS
2
Refrigerated Liquid, USP
UN1073 OXYGEN
Produced by
Air Liquefaction
M.D.D. Representative:
Medical Product Services
Borngassse 20
35619 Braunfels, Germany
CE 0029
CS087

PACKAGE LABEL

HELIOS
OXYGEN
REFRIGERATED
LIQUID-USP
UN1073
BY AIR LIQUEFACTION
OXYGEN
2
CS073

PACKAGE LABEL

COMPANION
OXYGEN,
REFRIGERATED
LIQUID-USP OXYGEN
UN 1073 2
BY AIR LIQUEFACTION
PART No
775252
REV. C